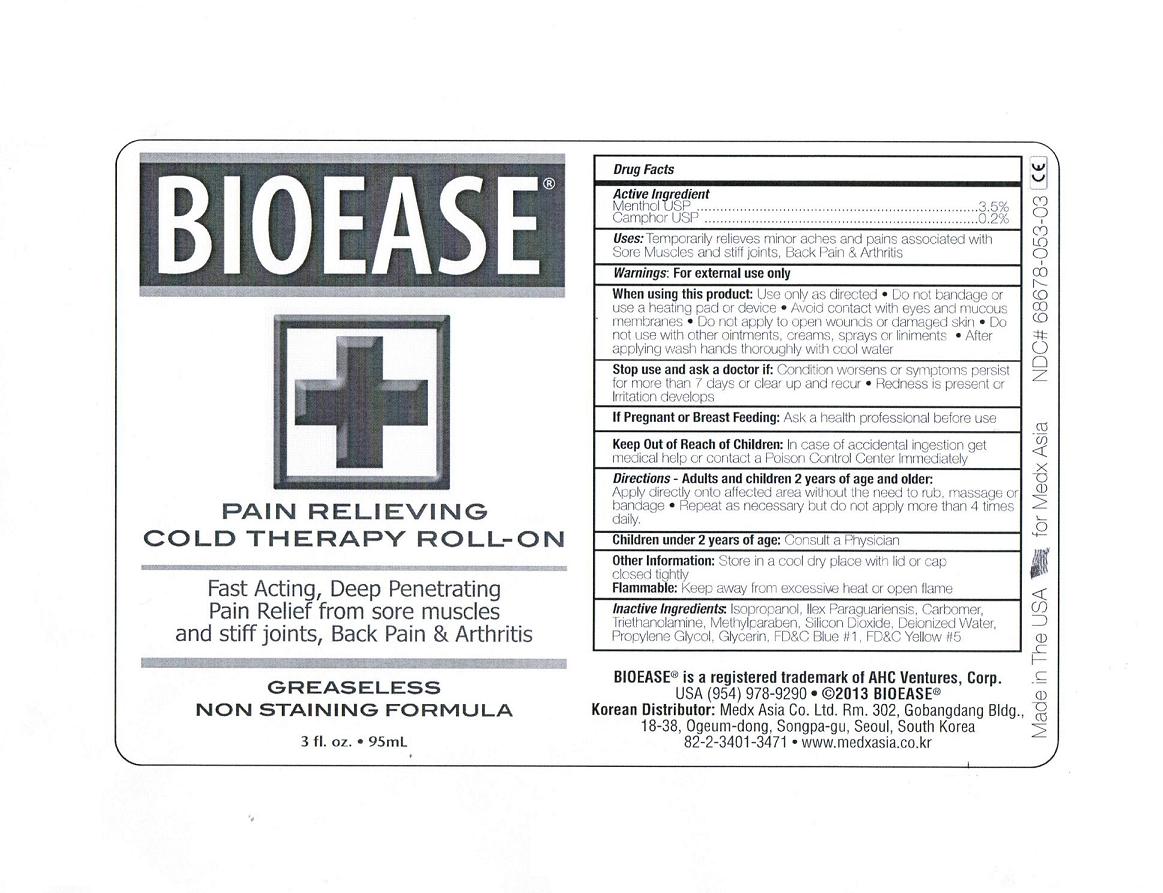 DRUG LABEL: BIOEASE PAIN RELIEVING COLD THERAPY
NDC: 68678-053 | Form: GEL
Manufacturer: AHC Ventures Corp DBA Cryoderm
Category: otc | Type: HUMAN OTC DRUG LABEL
Date: 20140202

ACTIVE INGREDIENTS: MENTHOL 3.5 g/100 mL; CAMPHOR (NATURAL) .2 g/100 mL
INACTIVE INGREDIENTS: ISOPROPYL ALCOHOL; ILEX PARAGUARIENSIS LEAF; CARBOMER COPOLYMER TYPE A (ALLYL PENTAERYTHRITOL CROSSLINKED); TROLAMINE; METHYLPARABEN; SILICON DIOXIDE; WATER; PROPYLENE GLYCOL; GLYCERIN; FD&C BLUE NO. 1; FD&C YELLOW NO. 6

BIOEASE® Pain Relieving Cold Therapy Roll-On

Active ingredient

Menthol USP……..3.5%
Camphor………….0.2%

Purpose

Pain Relief

Uses

Temporarily relieves minor aches and pains associated with • sore muscles and stiff joints • back pain • arthritis

Warnings

For external use only

When using this product: Use only as directed • Do not bandage or use a heating pad or device • Avoid contact with eyes and mucous membranes • Do not apply to open wounds or damaged skin • Do not use with other ointments, creams, sprays or liniments • After applying wash hands thoroughly with cool water

Stop use and ask a doctor if: Condition worsens or symptoms persist for more than 7 days or clear up and recur • Redness is present or irritation develops

Pregnancy or Breast Feeding

Ask a health professional before use

Keep Out of Reach of Children

In case of accidental ingestion get medical help or contact a Poison Control Center immediately

Directions

Adults and children 2 years of age and older: Apply directly onto affected area without the need to rub, massage or bandage • Repeat as necessary but do not apply more than 4 times daily.

Children under 2 years of age: Consult a Physician

Storage and Handling

Store in a cool dry place with lid or cap closed tightly

Inactive Ingredients

Isopropanol, Ilex Paraguariensis, Carbomer, Triethanolamine, Methylparaben, Silicon Dioxide, Deionized Water, Propylene Glycol, Glycerin, FD&C Blue #1, FD&C Yellow #5